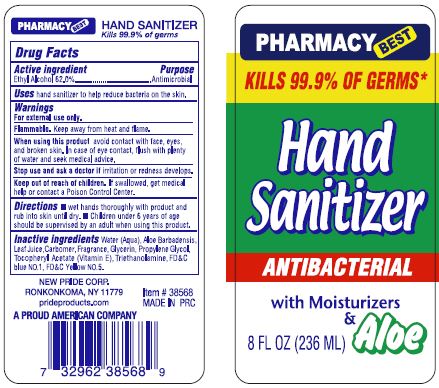 DRUG LABEL: HAND SANITIZER
NDC: 58037-102 | Form: GEL
Manufacturer: Pride Products Corp.
Category: otc | Type: HUMAN OTC DRUG LABEL
Date: 20220113

ACTIVE INGREDIENTS: ALCOHOL 62 mL/100 mL
INACTIVE INGREDIENTS: ALOE VERA LEAF; CARBOMER HOMOPOLYMER, UNSPECIFIED TYPE; GLYCERIN; PROPYLENE GLYCOL; .ALPHA.-TOCOPHEROL ACETATE; TROLAMINE; FD&C BLUE NO. 1; FD&C YELLOW NO. 5

PRIDE PRODUCTS - HAND SANITIZER (58037-102)

ACTIVE INGREDIENT

ETHYL ALCOHOL 62.0%

PURPOSE

ANTIMICROBIAL

USES

HAND SANITIZER TO HELP REDUCE BACTERIA ON THE SKIN

WARNINGS

FOR EXTERNAL USE ONLY

FLAMMABLE. KEEP AWAY FROM HEAT AND FLAME.

WHEN USING THIS PRODUCT AVOID CONTACT WITH FACE, EYES, AND BROKEN SKIN. IN CASE OF EYE CONTACT, FLUSH WITH PLENTY OF WATER AND SEEK MEDICAL ADVICE.

STOP USE AND ASK A DOCTOR IF IRRITATION OR REDNESS DEVELOPS.

Keep out of reach of children. If swallowed, get medical help or contact a Poison Control Center.

DIRECTIONS

- WET HANDS THOROUGHLY WITH PRODUCT AND RUB INTO SKIN UNTIL DRY.
- CHILDREN UNDER 6 YEARS OF AGE SHOULD BE SUPERVISED BY AN ADULT WHEN USING THIS PRODUCT.

INACTIVE INGREDIENTS

WATER (AQUA), ALOE BARBADENSIS LEAF JUICE, CARBOMER, FRAGRANCE, GLYCERIN, PROPYLENE GLYCOL, TOCOPHERYL ACETATE (VITAMIN E), TRIETHANOLAMINE, FD&C BLUE NO. 1, FD&C YELLOW NO. 5.